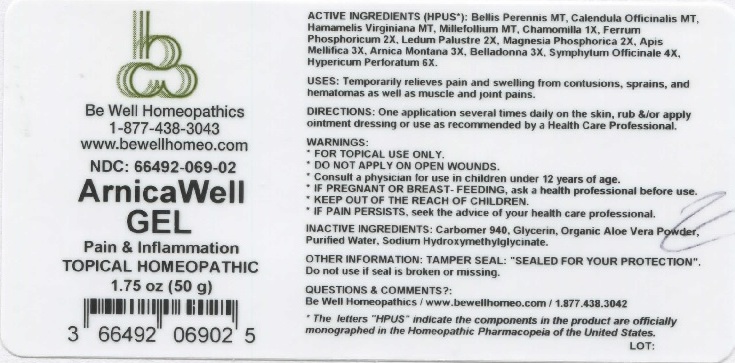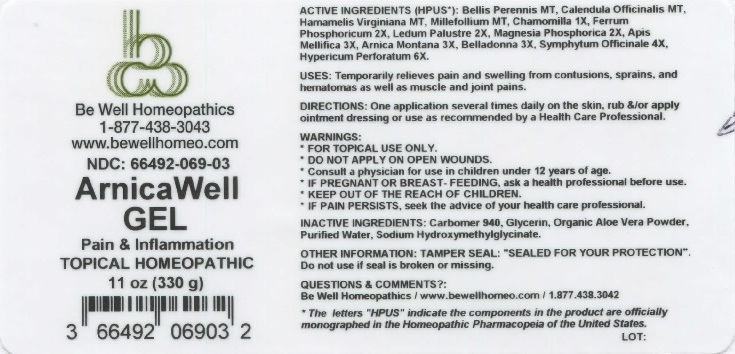 DRUG LABEL: Arnica Well
NDC: 66492-069 | Form: GEL
Manufacturer: Be Well Medical dba Richard Clement Nutrition y Be Well Homeopathics 052584997
Category: homeopathic | Type: HUMAN OTC DRUG LABEL
Date: 20211229

ACTIVE INGREDIENTS: BELLIS PERENNIS 1 [hp_X]/1 g; CALENDULA OFFICINALIS FLOWERING TOP 1 [hp_X]/1 g; HAMAMELIS VIRGINIANA ROOT BARK/STEM BARK 1 [hp_X]/1 g; ACHILLEA MILLEFOLIUM 1 [hp_X]/1 g; MATRICARIA CHAMOMILLA 1 [hp_X]/1 g; FERROSOFERRIC PHOSPHATE 2 [hp_X]/1 g; RHODODENDRON TOMENTOSUM LEAFY TWIG 2 [hp_X]/1 g; MAGNESIUM PHOSPHATE, DIBASIC TRIHYDRATE 2 [hp_X]/1 g; APIS MELLIFERA 3 [hp_X]/1 g; ARNICA MONTANA 3 [hp_X]/1 g; ATROPA BELLADONNA 3 [hp_X]/1 g; COMFREY ROOT 4 [hp_X]/1 g; HYPERICUM PERFORATUM 6 [hp_X]/1 g
INACTIVE INGREDIENTS: CARBOMER 940; GLYCERIN; ALOE VERA LEAF; WATER; SODIUM HYDROXYMETHYLGLYCINATE

Arnica Well Gel

ACTIVE INGREDIENT

ACTIVE INGREDIENTS (HPUS*): Bellis Perennis MT, Calendula Officinalis MT, Hamamelis Virginiana MT, Millefollium MT, Chamomilla 1X, Ferrum Phosphoricum 2X, Ledum Palustre 2X, Magnesia Phosphorica 2X, Apis Mellifica 3X, Arnica Montana 3X, Belladonna 3X, Symphytum Officinale 4X, Hypericum Perforatum 6X.

*The letters "HPUS" indicate that the components in the product are officially monographed in the Homeopathic Pharmacopeia of the United States.

INDICATIONS AND USAGE

USES: Temporarily relieves pain and swelling from contusions, sprains, and hematomas as well as muscle and joint pains.

WARNINGS:

- FOR TOPICAL USE ONLY.
- DO NOT APPLY ON OPEN WOUNDS.
- Consult a physician for use in children under 12 years of age.
- IF PREGNANT OR BREAST-FEEDING, ask a health professional before use.
- IF PAIN PERSISTS, seek the advice of your health care professional.

KEEP OUT OF THE REACH OF CHILDREN.

DOSAGE AND ADMINISTRATION

DIRECTIONS: One application several times daily on the skin, rub &/or apply ointment dressing or use as recommended by a Health Care Professional.

OTHER INFORMATION: TAMPER SEAL: "SEALED FOR YOUR PROTECTION". Do not use if seal is broken or missing.

INACTIVE INGREDIENT

INACTIVE INGREDIENTS: Carbomer 940, Glycerin, Organic Aloe Vera Powder, Purified Water, Sodium Hydroxymethylglycinate.

QUESTIONS

QUESTIONS & COMMENTS?: Be Well Homeopathics / www.bewellhomeo.com / 1.877.438.3042

PACKAGE LABEL

Be Well Homeopathics

1-877-438-3043

www.bewellhomeo.com

NDC: 66492-069-02

NDC: 66492-069-03

Arnica Well GEL

TOPICAL HOMEOPATHIC

1.75 oz (50 g)

11 oz (330 g)

PURPOSE

Pain & Inflammation